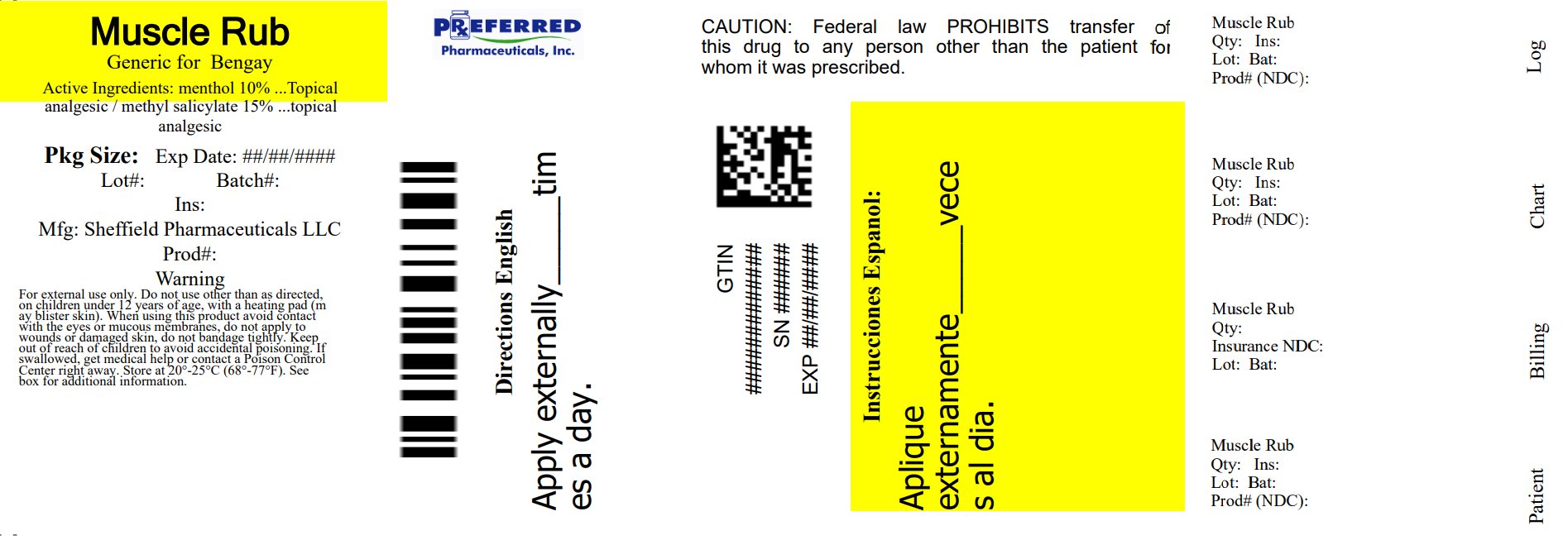 DRUG LABEL: Rugby Muscle Rub Cream
NDC: 68788-8729 | Form: CREAM
Manufacturer: Preferred Pharmaceuticals Inc.
Category: otc | Type: HUMAN OTC DRUG LABEL
Date: 20250818

ACTIVE INGREDIENTS: MENTHOL, UNSPECIFIED FORM 100 mg/1 g; METHYL SALICYLATE 150 mg/1 g
INACTIVE INGREDIENTS: CARBOMER HOMOPOLYMER TYPE C (ALLYL PENTAERYTHRITOL CROSSLINKED); CETYL ALCOHOL; TROLAMINE; WATER; STEARIC ACID; OLETH-3 PHOSPHATE

Active Ingredients

Menthol - 10%

Methyl salicylate - 15%

Purpose

Topical Analgesic

Topical Analgesic

Uses

- For temporary relief of minor aches and pains of muscle and joints associated with simple backaches, arthritis, strains, bruises and sprains

Warnings

For external use only

Avoid contact with eyes and mucous membranes

- If conditions worsens, or if symtoms persist for more than 7 days or clear up and occur again within a few days, discontinue use of this product and consult a doctor.
- Do not apply to wounds or damaged skin.
- Do not apply bandage tightly.
- Do not use with a heating pad or on wounds, damaged, broken (open) or irritated skin.
- Discontinue use if excessive irritation of skin develops.
- If pregnant or breast feeding, ask a health professional before use.
- A temporary burning sensation may occur upon application, but generally disappears in a few days.

KEEP OUT OF REACH OF CHILDREN

Keep this and all drugs out of the reach of children. If swallowed, get medical help or contact a Poison Control Center immediately.

Directions

- Adults and children 2 years of age and older; Apply to affected area not more than 3 to 4 times daily. Children under 2 years of age; consult a doctor.
- Unless treating hands, wash hands throughly with soap and water immediately after use.

Other information

Store at controlled room temperature 68°- 77°F (20° to 25°C) Close cap tightly afteruse.

Inactive ingredients

Carbomer, Cetyl Alcohol, Oleth-3 Phosphate, Stearic acid, Triethanolamine, Purified Water

Principal Display Panel - 3.0 oz Carton

Rugby

Greaseless

MUSCLE RUB Cream

10% Menthol / 15% Methyl Salicylate

Topical Analgesic

Net WT. 3.0 OZ (85g)

Relabeled By: Preferred Pharmaceuticals Inc.

68788-8729-8